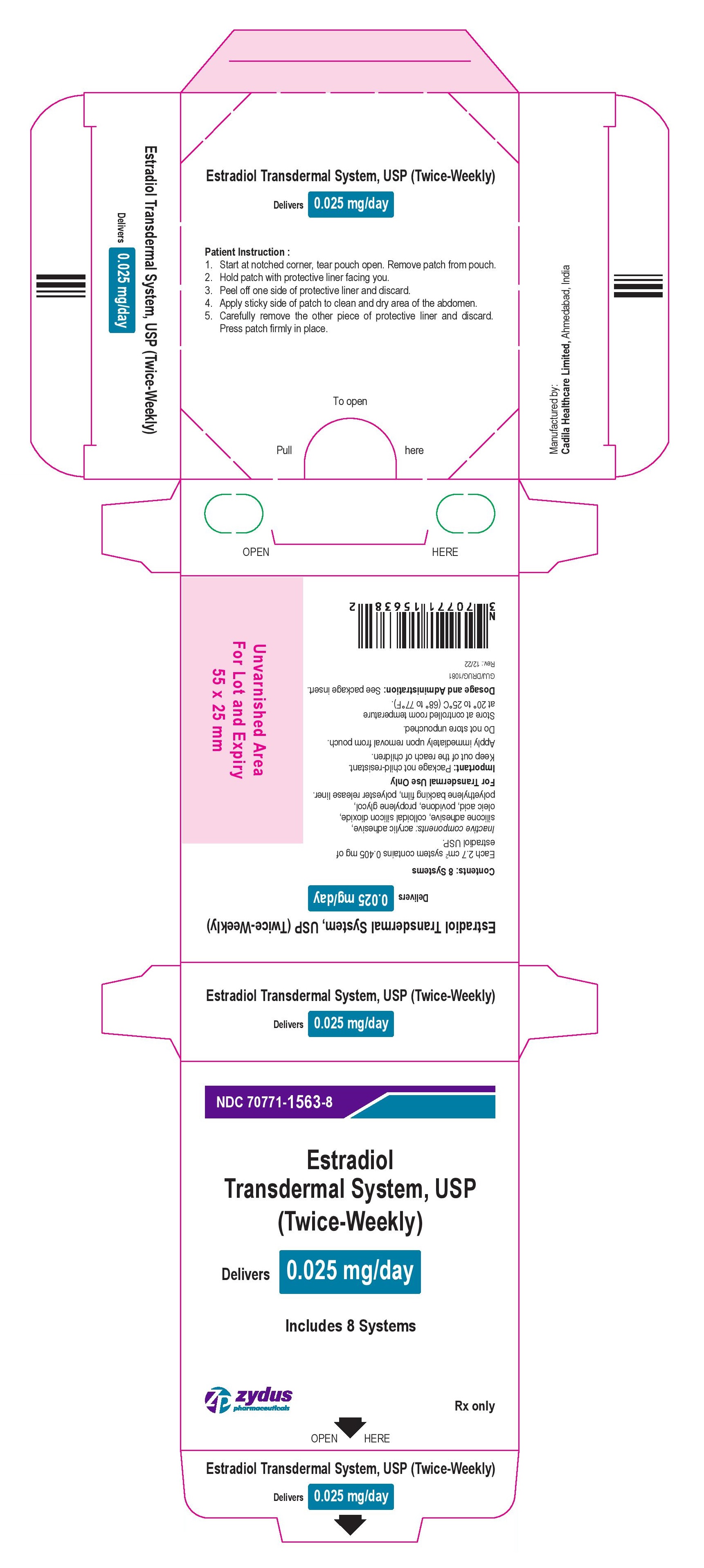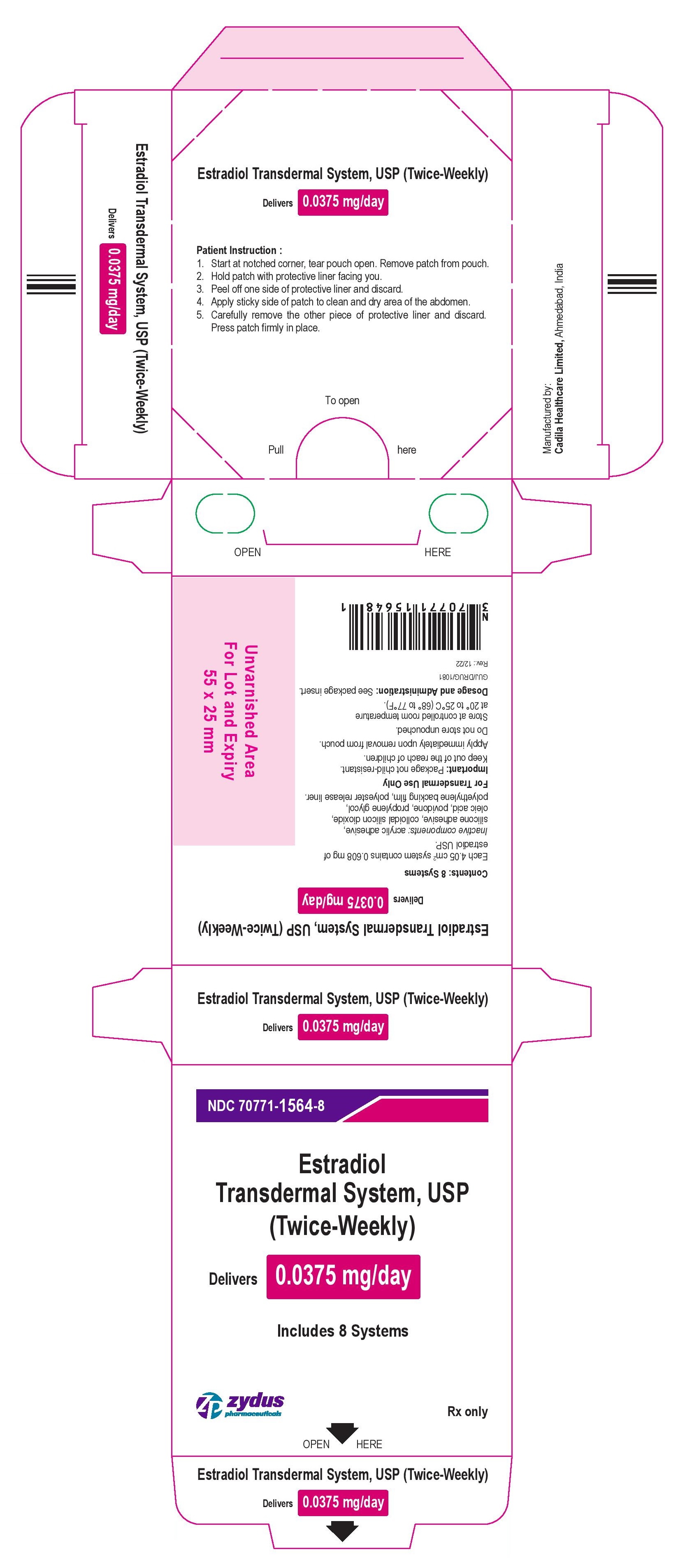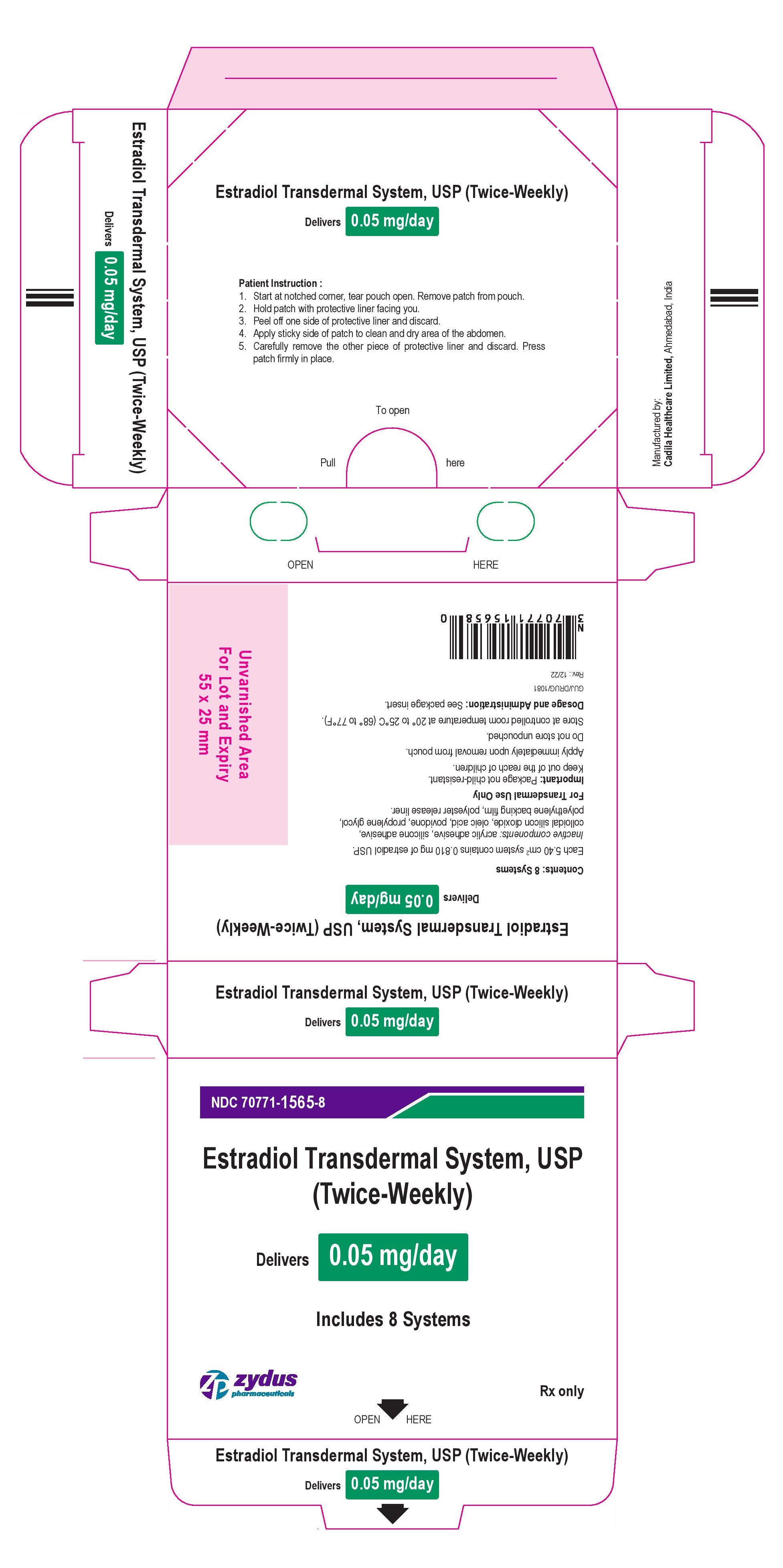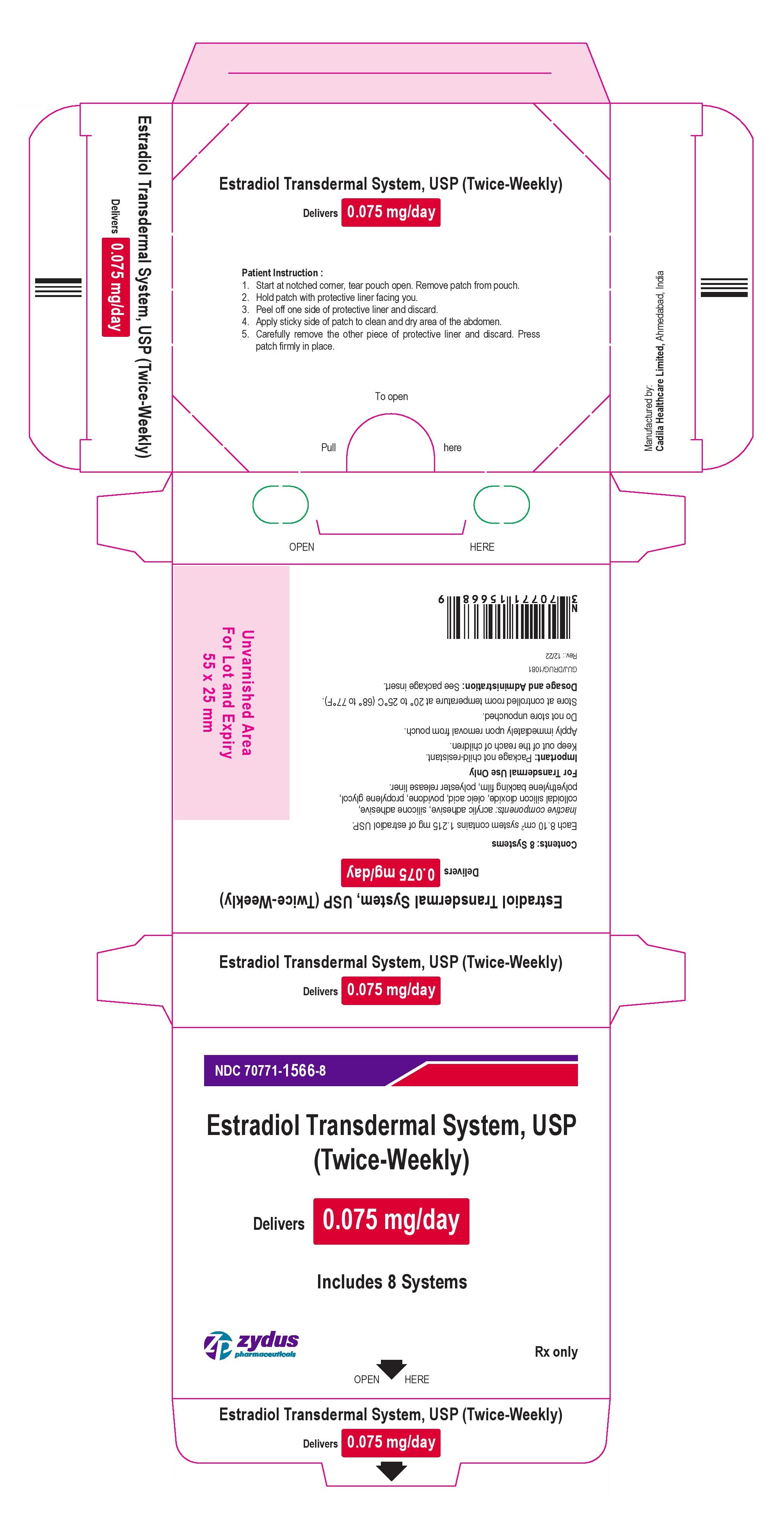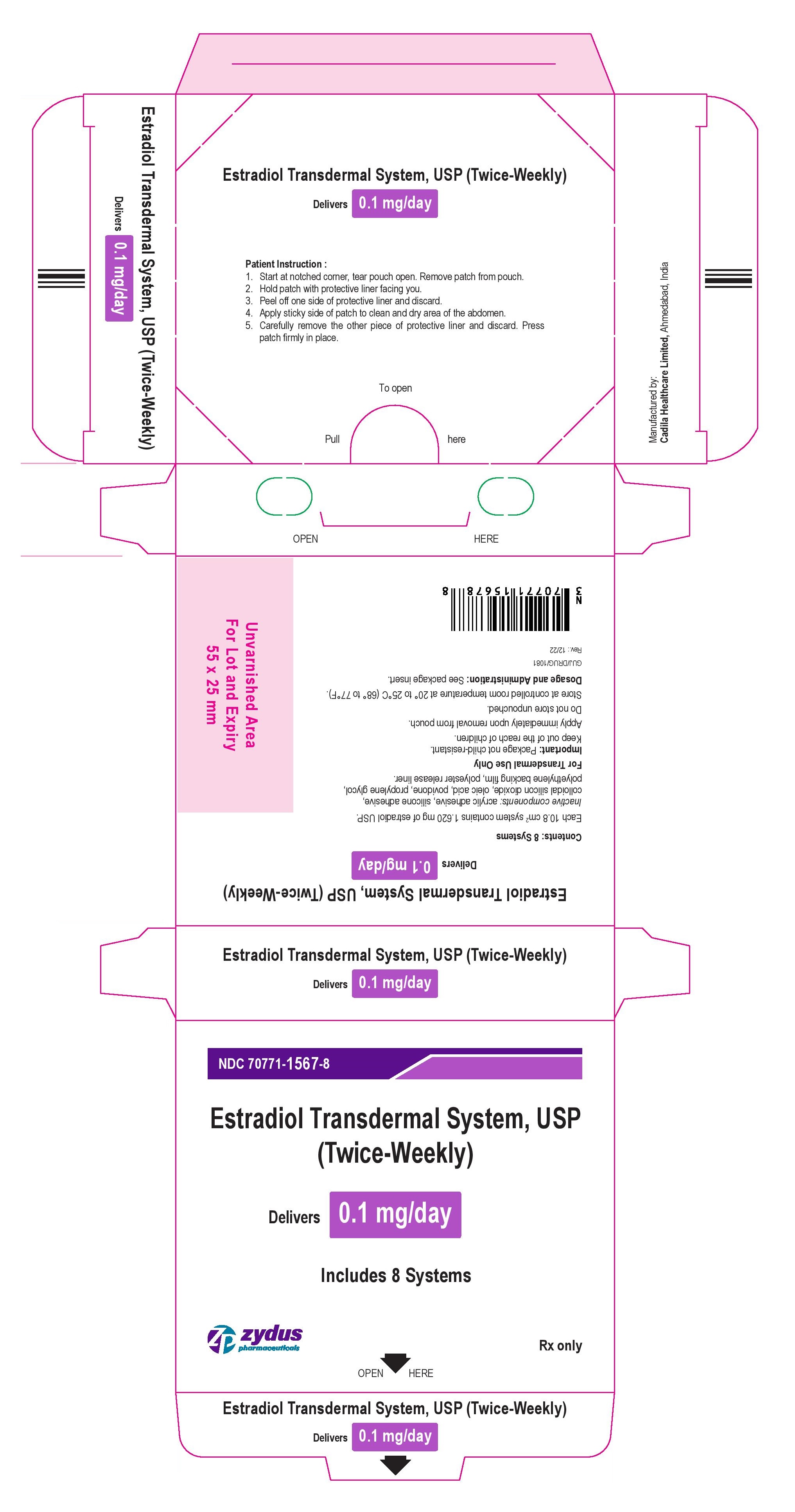 DRUG LABEL: Estradiol
NDC: 70771-1563 | Form: PATCH, EXTENDED RELEASE
Manufacturer: Zydus Lifesciences Limited
Category: prescription | Type: HUMAN PRESCRIPTION DRUG LABEL
Date: 20221207

ACTIVE INGREDIENTS: ESTRADIOL 0.025 mg/1 d
INACTIVE INGREDIENTS: OLEIC ACID; POVIDONE; PROPYLENE GLYCOL; SILICON DIOXIDE

ESTRADIOL transdermal system, USP (TWICE-WEEKLY)

PACKAGE LABEL.PRINCIPAL DISPLAY PANEL

Package Label – 0.025 mg

NDC 70771-1563-8

Estradiol Transdermal System, USP

(Twice-Weekly)

Delivers 0.025 mg/day

Includes 8 Systems

Rx Only

zydus pharmaceuticals

PACKAGE LABEL.PRINCIPAL DISPLAY PANEL

Package Label – 0.0375 mg

NDC 70771-1564-8

Estradiol Transdermal System, USP

(Twice-Weekly)

Delivers 0.0375 mg/day

Includes 8 Systems

Rx Only

zydus pharmaceuticals

PACKAGE LABEL.PRINCIPAL DISPLAY PANEL

Package Label – 0.05 mg

NDC 70771-1565-8

Estradiol Transdermal System, USP

(Twice-Weekly)

Delivers 0.05 mg/day

Includes 8 Systems

Rx Only

zydus pharmaceuticals

PACKAGE LABEL.PRINCIPAL DISPLAY PANEL

Package Label – 0.075 mg

NDC 70771-1566-8

Estradiol Transdermal System, USP

(Twice-Weekly)

Delivers 0.075 mg/day

Includes 8 Systems

Rx Only

zydus pharmaceuticals

PACKAGE LABEL.PRINCIPAL DISPLAY PANEL

Package Label – 0.1 mg

NDC 70771-1567-8

Estradiol Transdermal System, USP

(Twice-Weekly)

Delivers 0.1 mg/day

Includes 8 Systems

Rx Only

zydus pharmaceuticals